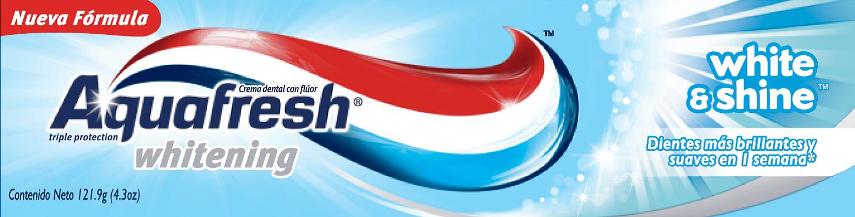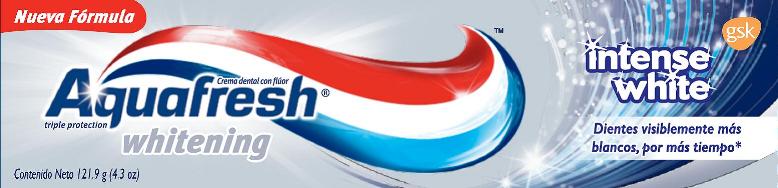 DRUG LABEL: AQUAFRESH whitening

NDC: 0135-0614 | Form: PASTE
Manufacturer: Haleon US Holdings LLC
Category: otc | Type: HUMAN OTC DRUG LABEL
Date: 20240424

ACTIVE INGREDIENTS: SODIUM FLUORIDE 1.5 mg/1 g
INACTIVE INGREDIENTS: WATER; SORBITOL; HYDRATED SILICA; GLYCERIN; SODIUM TRIPOLYPHOSPHATE ANHYDROUS; POLYETHYLENE GLYCOL 400; SODIUM LAURYL SULFATE; TITANIUM DIOXIDE; ALUMINUM OXIDE; XANTHAN GUM; COCAMIDOPROPYL BETAINE; CARRAGEENAN; SACCHARIN SODIUM; SODIUM HYDROXIDE; HIGH DENSITY POLYETHYLENE

Drug Facts

Purpose

Oral, helps prevents cavity

Directions

Brush teeth twice a day, and no more than three times, avoid swallowing. Spit out after brushing.

Warnings

Always follow the label. Do not use in children under 7 years of age.

Like other toothpastes, discontinue use if irritation or adverse reaction occurs. Consult a dentist if using fluoride supplements.

Store below 30°C.

Active ingredient

Sodium fluoride (sodium fluoride 0.15%) (1150 ppm of ion).

Contains Sodium Fluoride

Inactive ingredients

Water; Sorbitol; Hydrated Silica; Glycerin; Pentasodium Triphosphate; PEG-8; Sodium Lauryl Sulfate; Flavor*; Titanium Dioxide; Alumina; Xanthan Gum; Cocamidopropyl betaine; Carrageenan; Sodium Saccharin; Sodium Hydroxide; Polyethylene; CI42090; CI73360.

*Contains d-limonene.

Principal Display Panel

NDC 0135-0613-01

Aquafresh®

whitening

Fluoride toothpaste

triple protection®

New Formula

white & shine

Brighter teeth in 1 week*

NET WT 121.9g (4.3oz)

Brighter teeth in just 1 week, thanks to the toothpaste Aquafresh White & Shine. Clinically proven*. Helps keep your teeth whiter and brighter for longer. Lasting whitening.

Protection to keep your mouth healthy and happy

*Compared to a standard toothpaste, with regular brushing

Made in the United States of America by: GlaxoSmithKline LLC, East Durham, NY 12423. Aquafresh® is a trademark of the GlaxoSmithKline group of companies.

Imported and distributed by:

GlaxoSmithKline Argentina S.A.,C. Casares 3690, Victoria, Bs.As., Argentina. Legajo N° 6557. M.S. Resol. N° 155/98. For questions: 0800 888-6006

GlaxoSmithKline Brasil Ltda.,Est. dos Bandeirantes, 8464, Rio de Janeiro, RJ. CNPJ33.247.743/0001-10. AFE: 2000086 Proc.: 25351080153201313. SAC 0800 021 15 29.

GlaxoSmithKline Chile Farmaceutica Ltda.,Lo Boza 107, Modulo A-6, Pudahuel, Santiago, Chile. Reg. I.S.P. N° 299C-38/13. For questions: 800382900.

Andean Region:Hansa Ltda., La Paz, Bolivia.

GlaxoSmithKline Colombia S.A.,Bogota, D.C., Colombia. For questions: 01-8000-118686.

GlaxoSmithKline Ecuador S.A.,Quito, Ecuador.

GlaxoSmithKline Peru S.A.,Av. Javier Prado Oeste 995, Peru. RUC 20100123682.

GlaxoSmithKline Costa Rica S.A.,400 mts. East of the Circle La Bandera, Sabanilla highway, San Jose, Costa Rica. Tel: 506 22066000.

GlaxoSmithKline Paraguay S.A., G. Aranda 333, Paraguay. Distributed by Helsecke y Cia. S.A.C.I. Req. Sanit. N°.

GlaxoSmithKline Uruguay S.A.,Salto 1105 Montevideo, Uruguay. Imp. N°10. Ley 15443. Reg. MSP N°.

GlaxoSmithKline Venezuela C.A.,Caracas, Venezuela. Registered under MPPS bajo NSO-PC-E-45.970-VE. RIF: J-00021492-1. Panama. Nicaragua. El Salvador. Honduras. Guatemala. Dominican Rep.

102938XA

Principal Display Panel

NDC 0135-0614-01

Aquafresh®

whitening

Fluoride toothpaste

triple protection®

New Formula

intense white

whiter teeth that last longer*

NET WT 121.9g (4.3oz)

Whiter teeth that last longer*. Smile with confidence in your visibly whiter teeth for longer-result clinically proven by Aquafresh Intense White*. Contains small particles to clean and visibly whiten your teeth. Creates a protective barrier that helps prevent movement and new stains.

Protection to keep your mouth healthy and happy

*Compared to a standard toothpaste, with regular brushing, as assessed by dentists.

Made in the United States of America by: GlaxoSmithKline LLC, East Durham, NY 12423. Aquafresh® is a trademark of the GlaxoSmithKline group of companies.

Imported and distributed by:

GlaxoSmithKline Argentina S.A.,C. Casares 3690, Victoria, Bs.As., Argentina. Legajo N° 6557. M.S. Resol. N° 155/98. For questions: 0800 888-6006

GlaxoSmithKline Brasil Ltda.,Est. dos Bandeirantes, 8464, Rio de Janeiro, RJ. CNPJ33.247.743/0001-10. AFE: 2000086 Proc.: 25351080153201313. SAC 0800 021 15 29.

GlaxoSmithKline Chile Farmaceutica Ltda.,Lo Boza 107, Modulo A-6, Pudahuel, Santiago, Chile. Reg. I.S.P. N° 299C-38/13. For questions: 800382900.

Andean Region:Hansa Ltda., La Paz, Bolivia.

GlaxoSmithKline Colombia S.A.,Bogota, D.C., Colombia. For questions: 01-8000-118686.

GlaxoSmithKline Ecuador S.A.,Quito, Ecuador.

GlaxoSmithKline Peru S.A.,Av. Javier Prado Oeste 995, Peru. RUC 20100123682.

GlaxoSmithKline Costa Rica S.A.,400 mts. East of the Circle La Bandera, Sabanilla highway, San Jose, Costa Rica. Tel: 506 22066000.

GlaxoSmithKline Paraguay S.A., G. Aranda 333, Paraguay. Distributed by Helsecke y Cia. S.A.C.I. Req. Sanit. N°.

GlaxoSmithKline Uruguay S.A.,Salto 1105 Montevideo, Uruguay. Imp. N°10. Ley 15443. Reg. MSP N°.

GlaxoSmithKline Venezuela C.A.,Caracas, Venezuela. Registered under MPPS bajo NSO-PC-E-45.970-VE. RIF: J-00021492-1. Panama. Nicaragua. El Salvador. Honduras. Guatemala. Dominican Rep.

We value your opinion

www.gsl.com102940XB